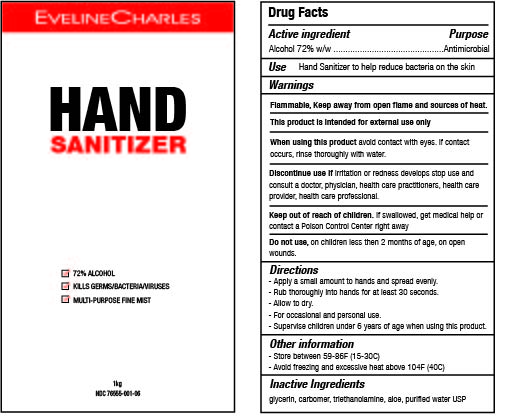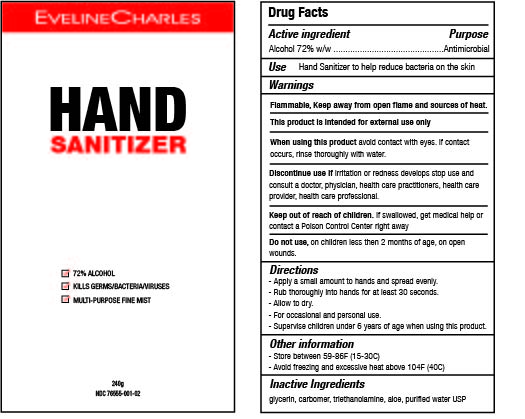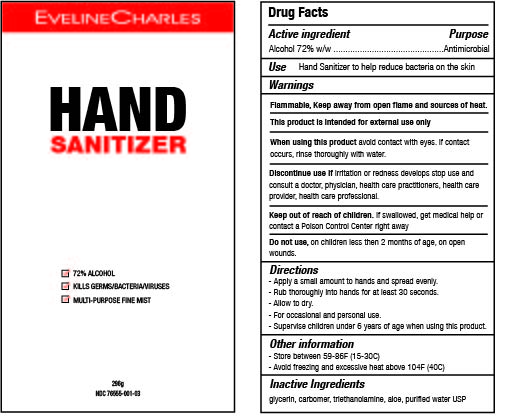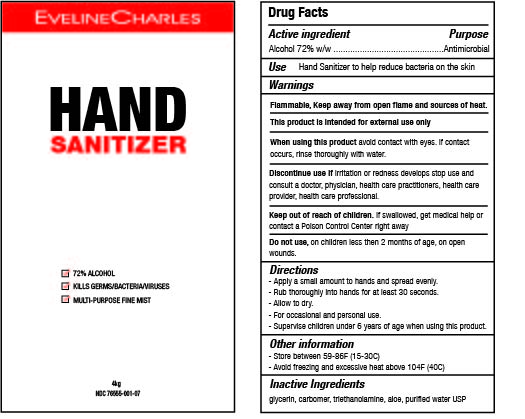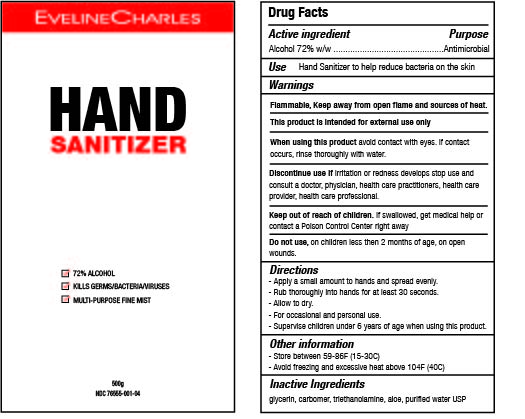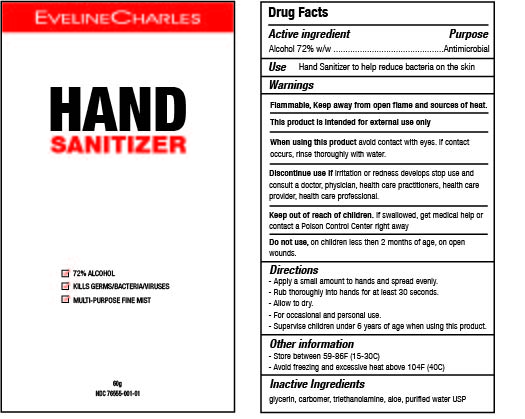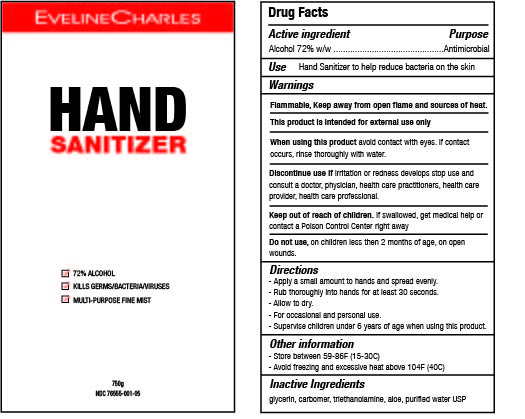 DRUG LABEL: Eveline Charles Hand Sanitizer
NDC: 76555-001 | Form: GEL
Manufacturer: Ec Labs Inc
Category: otc | Type: HUMAN OTC DRUG LABEL
Date: 20200605

ACTIVE INGREDIENTS: ALCOHOL 72 g/100 g
INACTIVE INGREDIENTS: GLYCERIN 2 g/100 g; ALOE VERA LEAF 0.05 g/100 g; WATER 25.15 g/100 g; CARBOMER 940 0.55 g/100 g; TROLAMINE 0.25 g/100 g

Eveline Charles Hand Sanitizerr

Hand sanitize eliminates bacteria, germs and viruses. Skin softening formula features aloe vera and glycerin for hydration and protection.

Active Ingredient(s)

Alcohol 72% w/w. Purpose: Antimicrobial

Purpose

Hand Sanitizer.

Use

Hand Sanitizer to kill harmful germs/bacteria/viruses. For use when soap and water are not available.

Warnings

For external use only

Flammability warning. Keep away from open flame and sources of heat
When using this product avoid contact with eyes. If contact occurs, rinse thoroughly with water.
Stop use and ask/ consult a doctor/ physician/ health care practitioner/ health care provider/ health care professional if irritation develops.
Keep out of reach of children. If swallowed, call a poison control centre or get medical help right away.

Do not use

- in children less than 2 months of age
- on open skin wounds

When using this product keep out of eyes, ears, and mouth. In case of contact with eyes, rinse eyes thoroughly with water.

Stop use and ask a doctor if irritation or rash occurs. These may be signs of a serious condition.

Keep out of reach of children. If swallowed, get medical help or contact a Poison Control Center right away.

Directions

- Apply a small amount to the hands and spread evenly. Rub thoroughly into hands for at least 30 seconds. Allow to dry. For occasional and personal domestic use.
- Supervise children under 6 years of age when using this product to avoid swallowing.

Other information

- Store between 15-30C (59-86F)
- Avoid freezing and excessive heat above 40C (104F)

Inactive ingredients

glycerin, carbomer, triethanolamine, aloe, purified water USP

PACKAGE LABEL

60g NDC: 76555-001-01

240g NDC: 76555-001-02

296g NDC: 76555-001-03

500g NDC: 76555-001-04

750g NDC: 76555-001-05

1kg NDC:76555-001-06

4kg NDC:76555-001-07